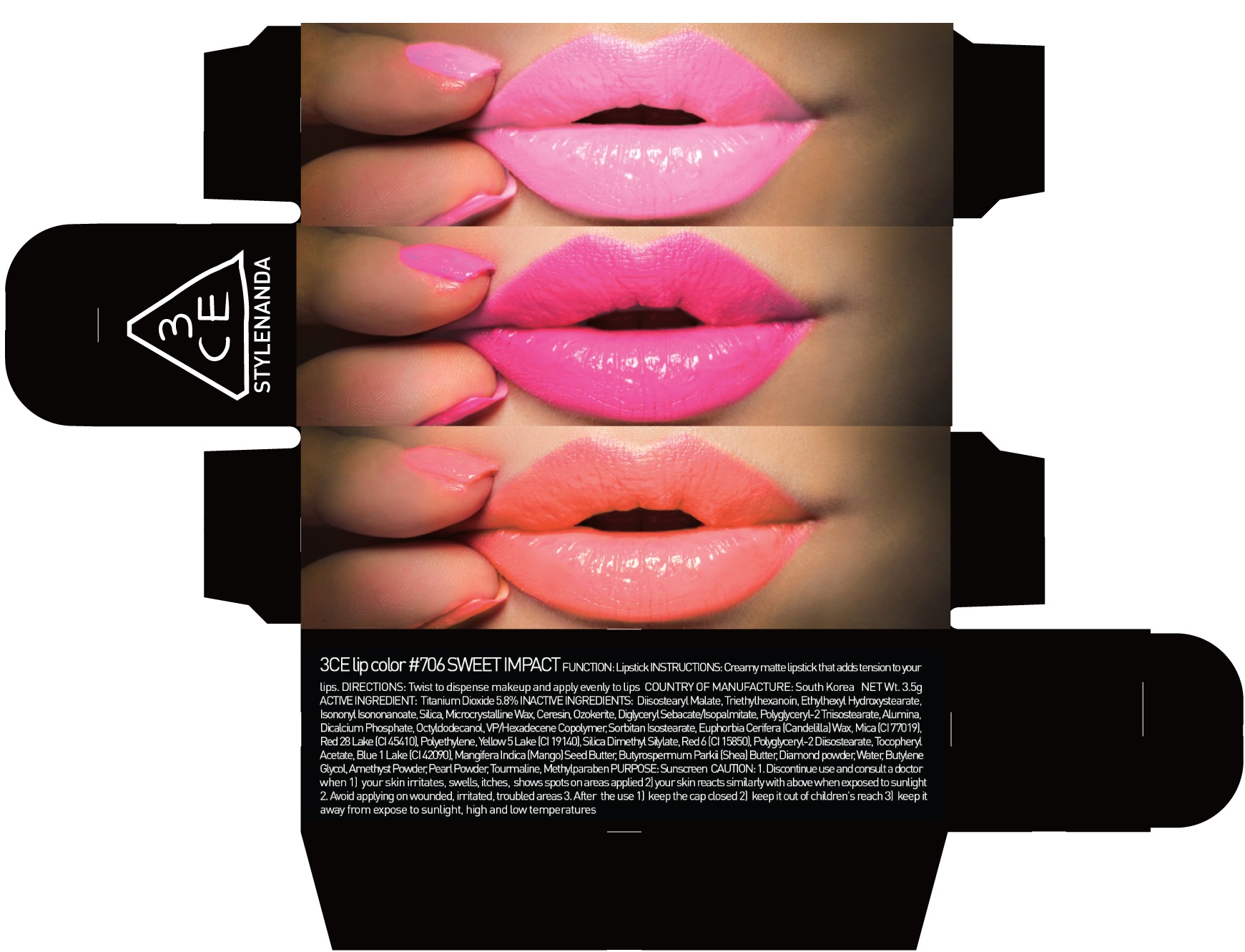 DRUG LABEL: 3CE LIP COLOR 706 SWEET IMPACT
NDC: 60764-083 | Form: LIPSTICK
Manufacturer: Nanda Co., Ltd
Category: otc | Type: HUMAN OTC DRUG LABEL
Date: 20161010

ACTIVE INGREDIENTS: Titanium Dioxide 0.20 g/3.5 g
INACTIVE INGREDIENTS: Diisostearyl Malate; Triethylhexanoin

ACTIVE INGREDIENT

Active Ingredient: Titanium Dioxide 5.8%

INACTIVE INGREDIENT

Inactive Ingredients: Diisostearyl Malate, Triethylhexanoin, EthylhexylHydroxystearate,IsononylIsononanoate, Silica, Microcrystalline Wax, Ceresin, Ozokerite, DiglycerylSebacate/Isopalmitate, Polyglyceryl-2 Triisostearate, Alumina, Dicalcium Phosphate, Octyldodecanol, VP/Hexadecene Copolymer, SorbitanIsostearate, Euphorbia Cerifera (Candelilla) Wax, Mica (CI 77019), Red 28 Lake (CI 45410), Polyethylene, Yellow 5 Lake (CI 19140), Silica Dimethyl Silylate, Red 6 (CI 15850), Polyglyceryl-2 Diisostearate, Tocopheryl Acetate, Blue 1 Lake (CI 42090), MangiferaIndica (Mango) Seed Butter, ButyrospermumParkii (Shea) Butter, Diamond powder, Water, Butylene Glycol, Amethyst Powder, Pearl Powder, Tourmaline, Methylparaben

PURPOSE

Purpose: Sunscreen

CAUTION

CAUTION: 1. Discontinue use and consult a doctor when - your skin irritates, swells, itches, shows spots on areas applied - your skin reacts similarly with above when exposed to sunlight 2. Avoid applying on wounded, irritated, troubled areas 3. After the use - keep the cap closed - keep it out of children's reach - keep it away from expose to sunlight, high and low temperatures

DESCRIPTION

INSTRUCTIONS: A rich color lipstick that moistly adheres to lips.

Directions: Twist to dispense makeup and apply evenly to lips